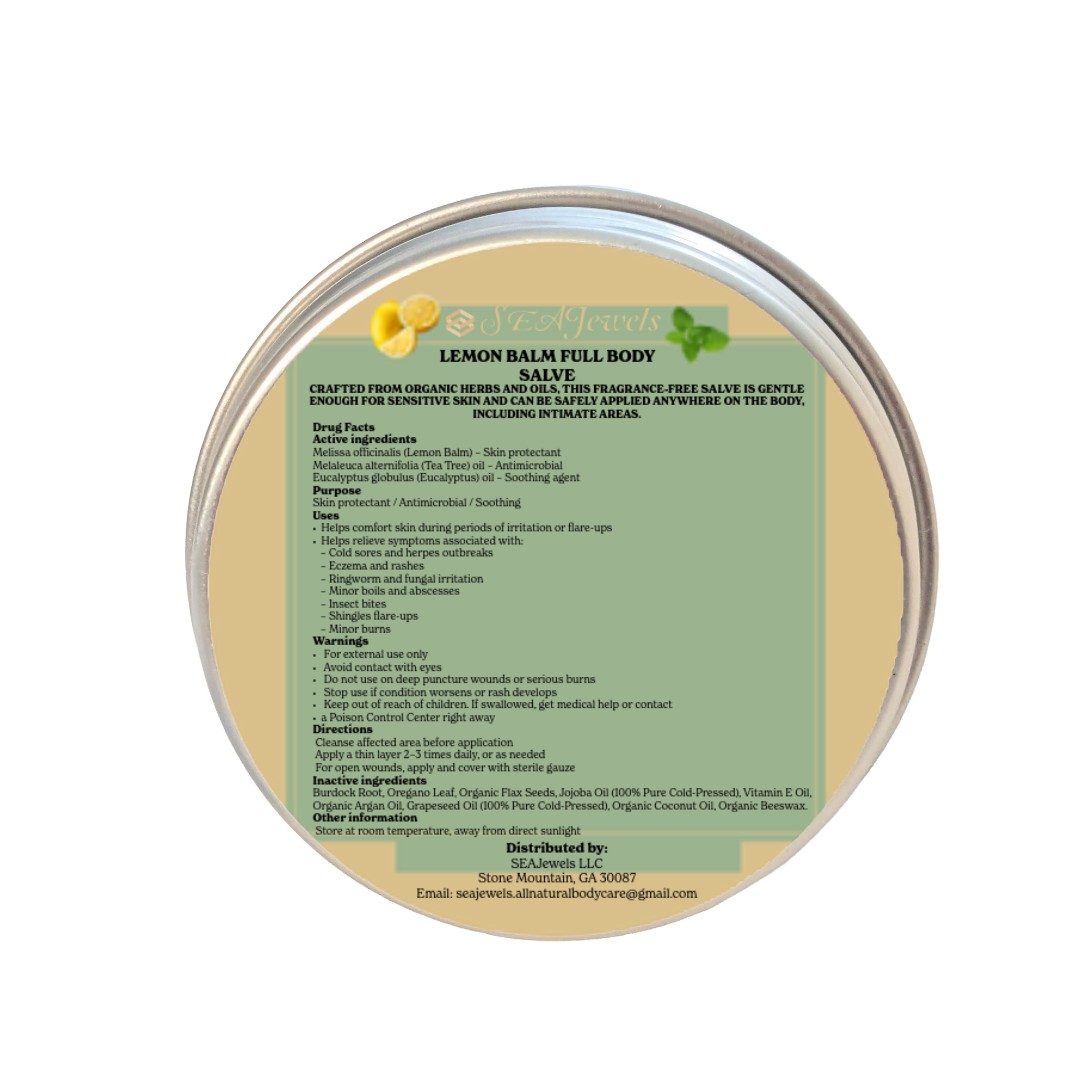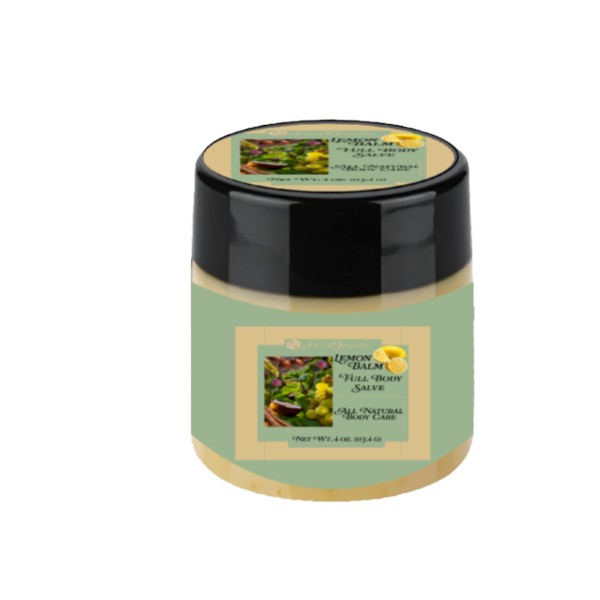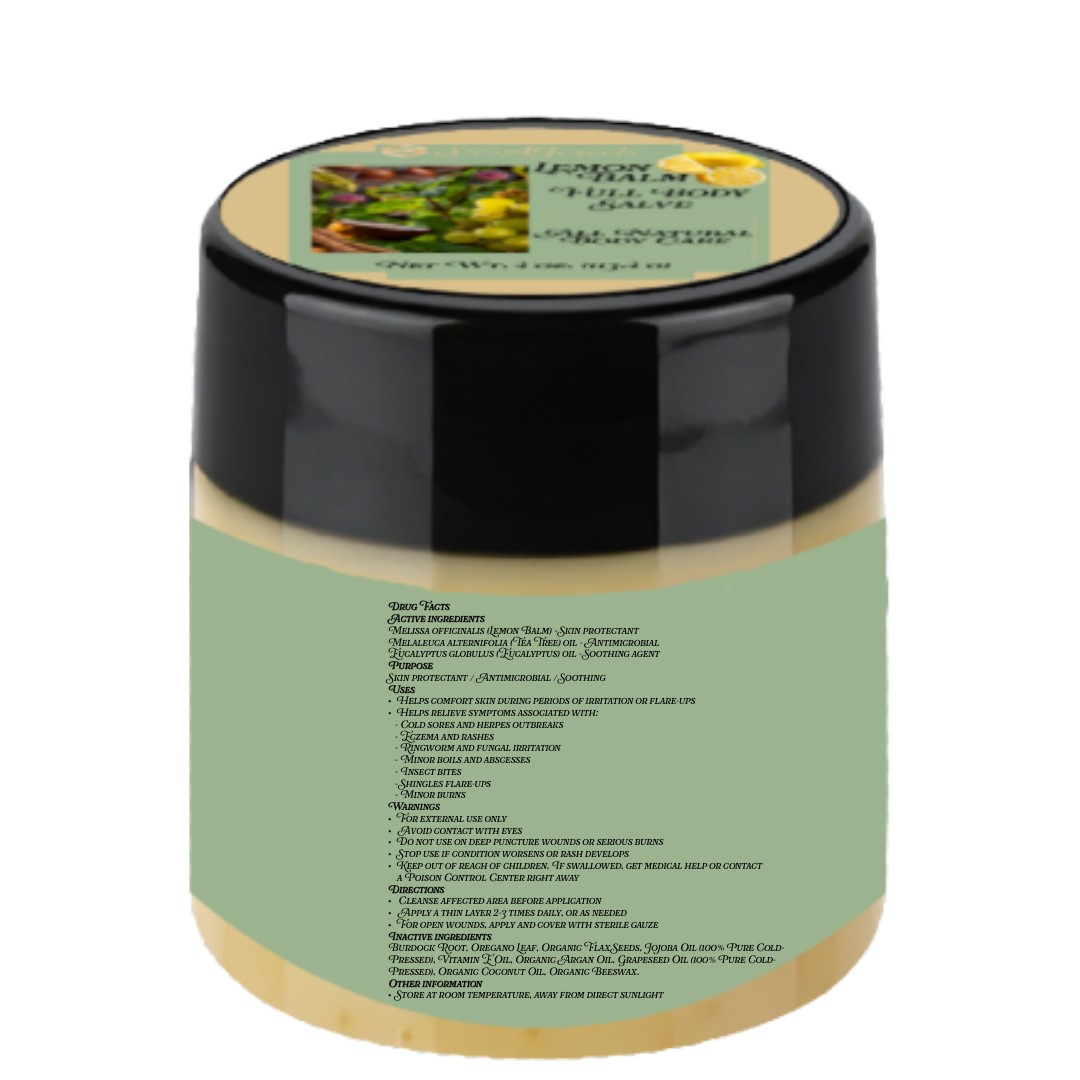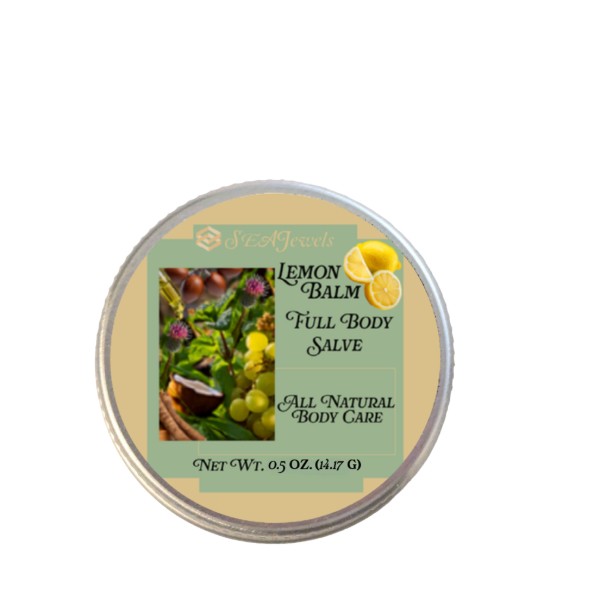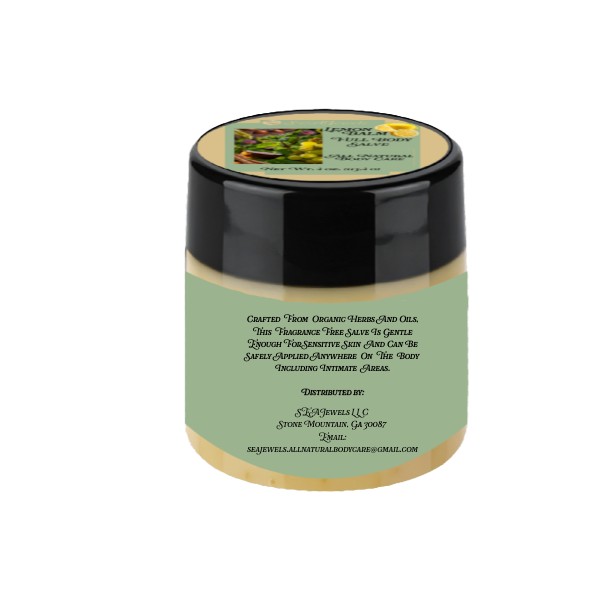 DRUG LABEL: Sea Jewels Lemon Balm Full Body Salve
NDC: 87060-001 | Form: SALVE
Manufacturer: SEAJewels LLC
Category: otc | Type: HUMAN OTC DRUG LABEL
Date: 20250820

ACTIVE INGREDIENTS: MELISSA OFFICINALIS LEAF 7 g/531.1 g; EUCALYPTUS OIL 2.3 g/531.1 g; MELALEUCA ALTERNIFOLIA (TEA TREE) LEAF OIL 2.2 g/531.1 g
INACTIVE INGREDIENTS: COCONUT OIL 28.35 g/531.1 g; BEESWAX 42.52 g/531.1 g; .ALPHA.-TOCOPHEROL ACETATE, DL- 1.2 g/531.1 g; FLAX SEED 42 g/531.1 g; ARGAN OIL 198.45 g/531.1 g; GRAPE SEED OIL 113.4 g/531.1 g; JOJOBA OIL 56.7 g/531.1 g; ARCTIUM LAPPA ROOT 30 g/531.1 g; OREGANO 7 g/531.1 g

Active Ingredients – Sea Jewels Lemon Balm Full Body Salve (0.5 oz)

Melissa officinalis (Lemon Balm) – Skin protectant
Melaleuca alternifolia (Tea Tree) oil – Antimicrobial
Eucalyptus globulus (Eucalyptus) oil – Soothing agent

See uploaded back label image.

Purpose – Sea Jewels Lemon Balm Full Body Salve (0.5 oz)

Skin protectant / Antimicrobial / Soothing

See uploaded back label image.

Indications & Usage – Sea Jewels Lemon Balm Full Body Salve (0.5 oz)

- Helps comfort skin during periods of irritation or flare-ups
- Helps relieve symptoms associated with:
• Cold sores and herpes outbreaks
• Eczema and rashes
• Ringworm and fungal irritation
• Minor boils and abscesses
• Insect bites
• Shingles flare-ups

• Minor burns

See uploaded back label image.

Warnings – Sea Jewels Lemon Balm Full Body Salve (0.5 oz)

For external use only

See uploaded back label image.

When Using – Sea Jewels Lemon Balm Full Body Salve (0.5 oz)

Avoid contact with eyes

See uploaded back label image.

Do Not Use – Sea Jewels Lemon Balm Full Body Salve (0.5 oz)

Do not use on deep puncture wounds or serious burns

See uploaded back label image.

Stop Use – Sea Jewels Lemon Balm Full Body Salve (0.5 oz)

Stop use if condition worsens or rash develops

See uploaded back label image.

Keep Out of Reach of Children – Sea Jewels Lemon Balm Full Body Salve (0.5 oz)

Keep out of reach of children. If swallowed, get medical help or contact a Poison Control Center right away

See uploaded back label image.

Dosage & Administration – Sea Jewels Lemon Balm Full Body Salve (0.5 oz)

- Cleanse affected area before application
- Apply a thin layer 2–3 times daily, or as needed
- For open wounds, apply and cover with sterile gauze

See uploaded back label image.

Inactive Ingredients – Sea Jewels Lemon Balm Full Body Salve (0.5 oz)

Burdock Root, Oregano Leaf, Organic Flax Seeds, Jojoba Oil (100% Pure Cold-Pressed), Vitamin E Oil, Organic Argan Oil, Grapeseed Oil (100% Pure Cold-Pressed), Organic Coconut Oil, Organic Beeswax

See uploaded back label image.

Other Safety Information – Sea Jewels Lemon Balm Full Body Salve (0.5 oz)

Store at room temperature, away from direct sunlight

See uploaded back label image.

Active Ingredients – Sea Jewels Lemon Balm Full Body Salve (4 oz)

Active ingredients

Melissa officinalis (Lemon Balm) – Skin protectant

Melaleuca alternifolia (Tea Tree) oil – Antimicrobial

Eucalyptus globulus (Eucalyptus) oil – Soothing agent

See uploaded back label image

Purpose – Sea Jewels Lemon Balm Full Body Salve (4 oz)

Skin protectant / Antimicrobial / Soothing

See uploaded back label image

Indications & Usage – Sea Jewels Lemon Balm Full Body Salve (4 oz)

Helps comfort skin during periods of irritation or flare-ups

Helps relieve symptoms associated with:
• Cold sores and herpes outbreaks
• Eczema and rashes
• Ringworm and fungal irritation
• Minor boils and abscesses
• Insect bites
• Shingles flare-ups
• Minor burns

See uploaded back label image.

Warnings – Sea Jewels Lemon Balm Full Body Salve (4 oz)

For external use only

See uploaded back label image.

When Using – Sea Jewels Lemon Balm Full Body Salve (4 oz)

Avoid contact with eyes.

See uploaded back label image.

Do Not Use – Sea Jewels Lemon Balm Full Body Salve (4 oz)

Do not use on deep puncture wounds or serious burns

See uploaded back label image.

Stop Use – Sea Jewels Lemon Balm Full Body Salve (4 oz)

Stop use if condition worsens or rash develops

See uploaded back label image.

Keep Out of Reach of Children – Sea Jewels Lemon Balm Full Body Salve (4 oz)

Keep out of reach of children. If swallowed, get medical help or contact a Poison Control Center right away.

See uploaded back label image.

Dosage & Administration – Sea Jewels Lemon Balm Full Body Salve (4 oz)

Cleanse affected area before application

Apply a thin layer 2–3 times daily, or as needed

For open wounds, apply and cover with sterile gauze

See uploaded back label image.

Inactive Ingredients – Sea Jewels Lemon Balm Full Body Salve (4 oz)

Burdock Root, Oregano Leaf, Organic Flax Seeds, Jojoba Oil (100% Pure Cold-Pressed),
Vitamin E Oil, Organic Argan Oil, Grapeseed Oil (100% Pure Cold-Pressed),
Organic Coconut Oil, Organic Beeswax

See uploaded back label image.

Other Safety Information – Sea Jewels Lemon Balm Full Body Salve (4 oz)

Store at room temperature, away from direct sunlight

See uploaded back label image.

Sea Jewels Lemon Balm Full Body Salve (0.5 oz) – Front Label

Sea Jewels Lemon Balm Full Body Salve
Net Wt. 14.17 g (0.5 oz)

See uploaded fron label images.

Sea Jewels Lemon Balm Full Body Salve (0.5 oz) – Back Label

Distributed by:
SEAJewels LLC
Stone Mountain, GA 30087
Email: seajewels.allnaturalbodycare@gmail.com

See uploaded back label image.

Sea Jewels Lemon Balm Full Body Salve (4 oz) – Front Label

Sea Jewels Lemon Balm Full Body Salve
Net Wt. 113.4 g (4 oz)

See uploaded front label image.

Sea Jewels Lemon Balm Full Body Salve (4 oz) – Side Label

Distributed by:
SEAJewels LLC
Stone Mountain, GA 30087
Email: seajewels.allnaturalbodycare@gmail.com

See uploaded side panel label image.